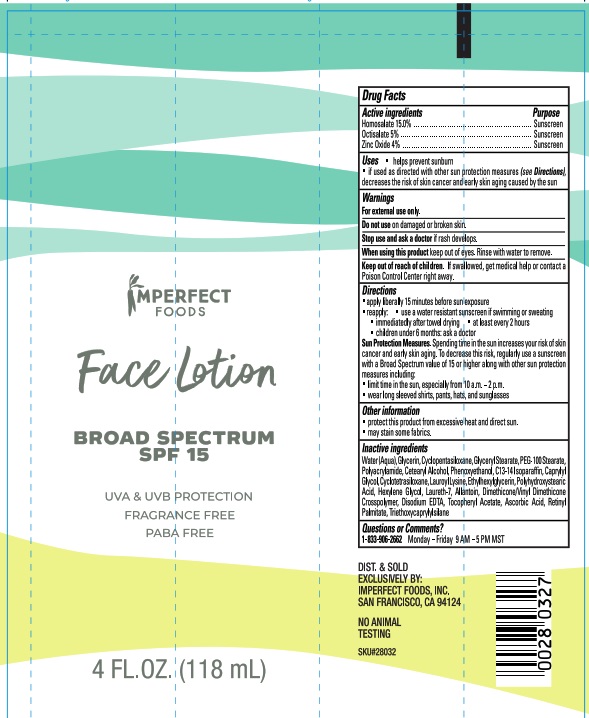 DRUG LABEL: Sunscreen
NDC: 81757-001 | Form: LOTION
Manufacturer: Imperfect Foods
Category: otc | Type: HUMAN OTC DRUG LABEL
Date: 20210419

ACTIVE INGREDIENTS: HOMOSALATE 15 g/100 mL; OCTISALATE 5 g/100 mL; ZINC OXIDE 4 g/100 mL
INACTIVE INGREDIENTS: C13-14 ISOPARAFFIN; STEARYL ALCOHOL; CAPRYLYL GLYCOL; PHENOXYETHANOL; POLYACRYLAMIDE (10000 MW); OCTAMETHYLTETRASILOXANE; LAURETH-7; WATER; GLYCERIN; DIMETHICONE/VINYL DIMETHICONE CROSSPOLYMER (SOFT PARTICLE); EDETATE DISODIUM; .ALPHA.-TOCOPHEROL ACETATE; ASCORBIC ACID; ALLANTOIN; POLYHYDROXYSTEARIC ACID (2300 MW); ETHYLHEXYLGLYCERIN; HEXYLENE GLYCOL; VITAMIN A PALMITATE; TRIETHOXYCAPRYLYLSILANE; PEG-100 STEARATE; CYCLOMETHICONE 5; LAUROYL LYSINE; CYCLOMETHICONE; GLYCERYL MONOSTEARATE

Active Ingredients

Homosalate 15%

Octisalate 5%

Zinc Oxide 4%

Uses

- Helps prevent sunburn
- If used as directed with other sun protection measures (see Directions) decreases the risk of skin cancer and early skin aging caused by the sun

Warnings

For external use only

Do not use

On damaged or broken skin

Ask a doctor

Stop use and ask a doctor if rash develops

When Using

When using this product keep out of eyes. Rinse with water to remove.

Keep out of reach of children. If swallowed, get medical help or contact a Poison Control Center right away.

Directions

- Apply liberally 15 minutes before sun exposure
- reapply: use a water resistant sunscreen if swimming or sweating
- immediately after towel drying
- at least every 2 hours
- children under 6 months: ask a doctor

Other Information

- Protect this product from excessive heat and direct sun
- may stain some fabrics

Inactive Ingredients

Water (Aqua), Glycerin, Cyclopentasiloxane, Glyceryl Stearate, PEG-100 Stearate, Polyacrylamide, Cetearyl Alcohol, Phenoxyethanol, C13-14 Isoparaffin, Caprylyl Glycol, Cyclotetrasiloxane, Lauroyl Lysine, Ethylhexylglycerin, Polyhydroxystearic Acid, Hexylene Glycol, Laureth-7, Allantoin, Dimethiconde/Vinyl Dimethicone Crosspolymer, Disodium EDTA, Tocopheryl Acetate, Ascorbic Acid, Retinyl Palmitate, Triethoxycaprylylsilane.

Questions or Comments?

1-833-906-2662 Monday - Friday 9AM-5PM MST

PACKAGE LABEL

SPF 15 Face Lotion NDC: 81757-001-04